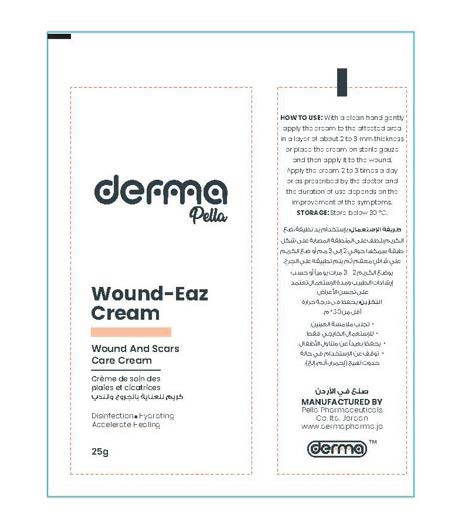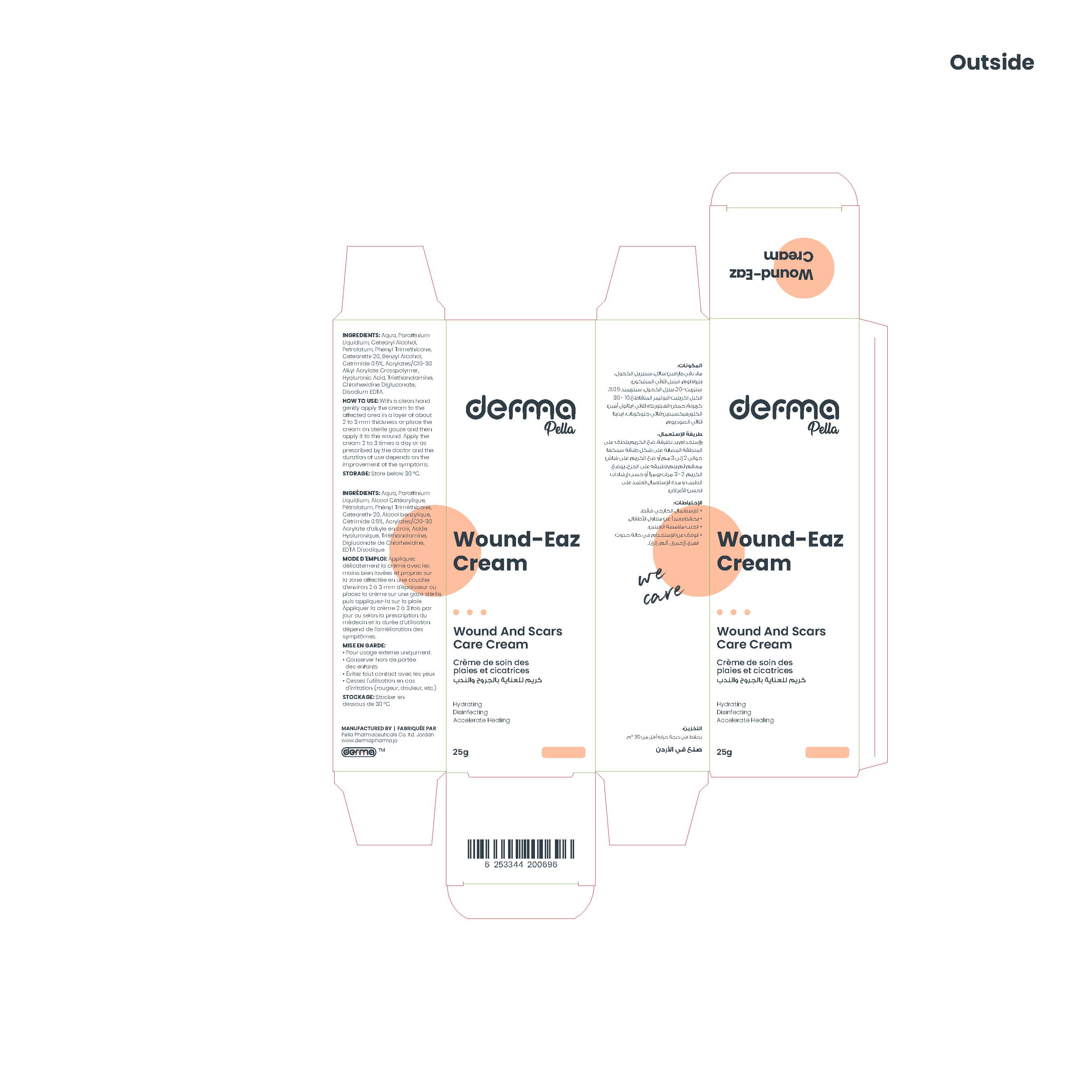 DRUG LABEL: Derma Wound-Eaz
NDC: 82160-696 | Form: CREAM
Manufacturer: Pella Pharmaceuticals Co. Ltd
Category: otc | Type: HUMAN OTC DRUG LABEL
Date: 20241231

ACTIVE INGREDIENTS: CETRIMIDE 5 mg/1 g
INACTIVE INGREDIENTS: CETOSTEARYL ALCOHOL; WATER; TROLAMINE; PETROLATUM; CARBOMER COPOLYMER TYPE B (ALLYL PENTAERYTHRITOL CROSSLINKED); BENZYL ALCOHOL; LIGHT MINERAL OIL; POLYOXYL 20 CETOSTEARYL ETHER; PHENYL TRIMETHICONE; EDETATE DISODIUM ANHYDROUS; HYALURONATE SODIUM; CHLORHEXIDINE GLUCONATE

Wound-Eaz

Form and Presentation

Cream: Laminated Tube, 25 g

Active Ingredient

Cetrimide

Inactive Ingredients

Aqua, Paraffinium Liquidium, Cetearyl Alcohol, Petrolatum, Phenyl Trimethicone, Ceteareth-20, Benzyl Alcohol, Acrylates/C10-30 Alkyl Acrylate Crosspolymer, Hyaluronic Acid, Triethanolamine, Chlorhexidine Digluconate, Disodium EDTA.

Purpose

Wound and scars care cream

Properties

This product is for the management of wounds and scars, it provides deep skin hydration, accelerates the process of regeneration. It works by softening and flattening raised scars of any kind and is an effective antiseptic with a wide range of activity against micro-organisms, including gram-positive and gram-negative bacteria, fungi, and viruses.

Indications

Used for the disinfection and healing of the wounds and burns and to reduce the appearance of scars that result from cuts and grazes, also used for dermatological disorders such as insect bites and stings, minor burns and scalds, sunburn, blisters and sores.

Precaution

Keep out of reach of children

Warnings

- For external use only.
- Avoid contact with eyes, if accidentally splashed into the eye, the open eye should be irrigated for at least 10 minutes.
- Discontinue use if irritation (redness, pain, etc.) occurs. If skin irritation occurs, consult your physician if the symptoms persist for more than 48 hr.

Contraindications

Hypersensitivity to any of the components.

Side Effects

Skin irritation.

Pregnancy and Lactation

There are no adequate data from the use of chlorhexidine digluconate and cetrimide in pregnant women.

The potential risk for humans is unknown but is most likely very low since chlorhexidine digluconate and cetrimide are poorly absorbed following topical application.

It is not known whether chlorhexidine digluconate and cetrimide are excreted in breast milk. There are no adequate data from the use of chlorhexidine and cetrimide in breastfeeding women. However, it is unlikely that the products are excreted in breast milk since the products are poorly absorbed. After topical usage of the product, as a general precaution, rinse nipples thoroughly with water before breastfeeding.

Dosage and Administration

With a clean hand gently apply the cream to the affected area in a layer of about 2 to 3 mm thickness or place the cream on sterile gauze and then apply it to the wound.

Apply the cream 2 to 3 times a day or as prescribed by the doctor and the duration of use depends on the improvement of the symptoms.

Interactions

The product is incompatible with anionic substances (e.g. soap, toothpaste).

Storage Conditions

Store below 30◦C